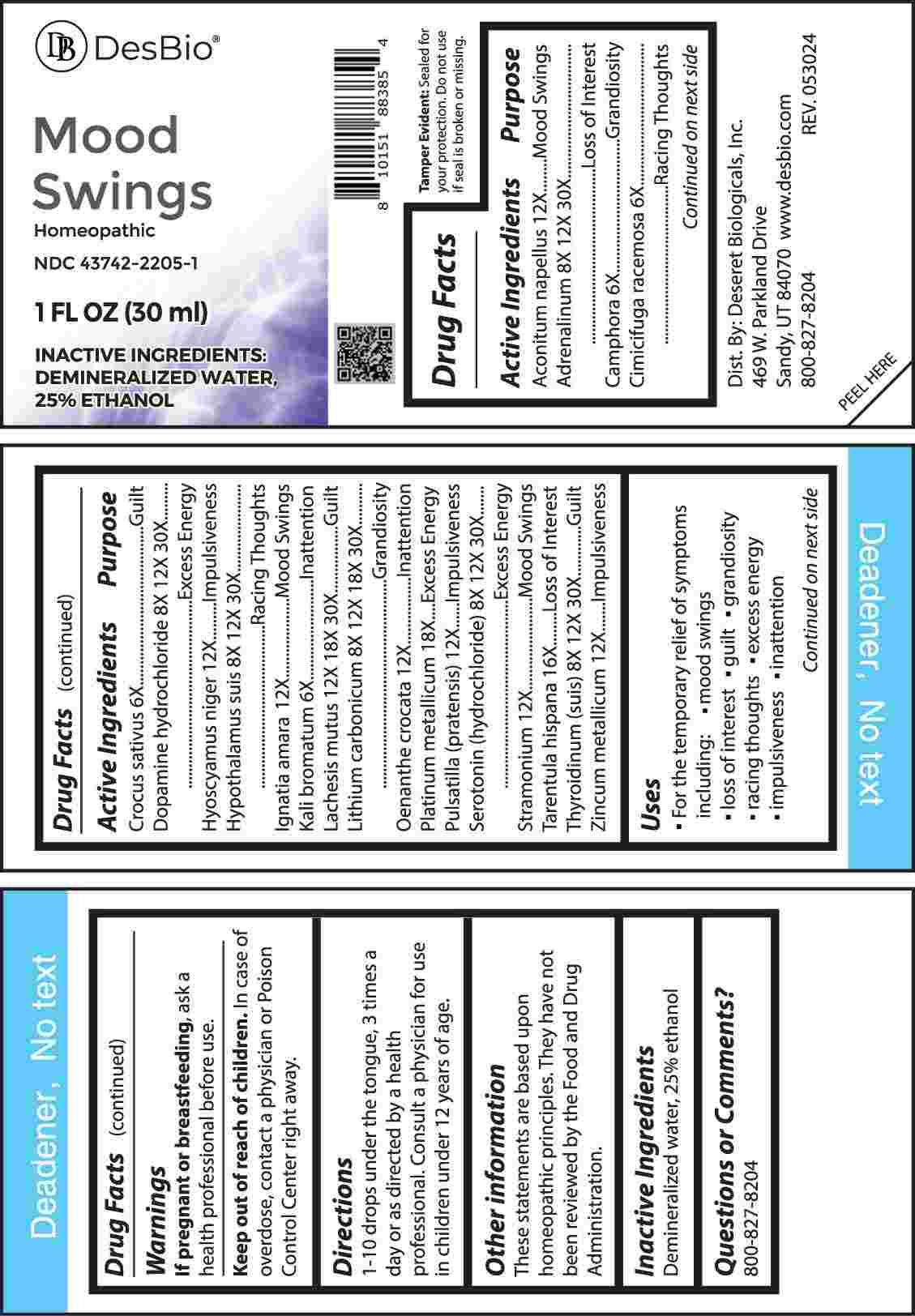 DRUG LABEL: Mood Swings
NDC: 43742-2205 | Form: LIQUID
Manufacturer: Deseret Biologicals, Inc.
Category: homeopathic | Type: HUMAN OTC DRUG LABEL
Date: 20241108

ACTIVE INGREDIENTS: ACONITUM NAPELLUS WHOLE 12 [hp_X]/1 mL; EPINEPHRINE 8 [hp_X]/1 mL; CAMPHOR (NATURAL) 6 [hp_X]/1 mL; BLACK COHOSH 6 [hp_X]/1 mL; SAFFRON 6 [hp_X]/1 mL; DOPAMINE HYDROCHLORIDE 8 [hp_X]/1 mL; HYOSCYAMUS NIGER 12 [hp_X]/1 mL; SUS SCROFA HYPOTHALAMUS 8 [hp_X]/1 mL; STRYCHNOS IGNATII SEED 12 [hp_X]/1 mL; POTASSIUM BROMIDE 6 [hp_X]/1 mL; LACHESIS MUTA VENOM 12 [hp_X]/1 mL; LITHIUM CARBONATE 8 [hp_X]/1 mL; OENANTHE CROCATA ROOT 12 [hp_X]/1 mL; PLATINUM 18 [hp_X]/1 mL; PULSATILLA PRATENSIS WHOLE 12 [hp_X]/1 mL; SEROTONIN HYDROCHLORIDE 8 [hp_X]/1 mL; DATURA STRAMONIUM 12 [hp_X]/1 mL; LYCOSA TARANTULA 16 [hp_X]/1 mL; THYROID 8 [hp_X]/1 mL; ZINC 12 [hp_X]/1 mL
INACTIVE INGREDIENTS: WATER; ALCOHOL

DRUG FACTS:

ACTIVE INGREDIENTS:

Aconitum Napellus 12X, Adrenalinum 8X, 12X, 30X, Camphora 6X, Cimicifuga Racemosa 6X, Crocus Sativus 6X, Dopamine Hydrochloride 8X, 12X, 30X, Hyoscyamus Niger 12X, Hypothalamus Suis 8X, 12X, 30X, Ignatia Amara 12X, Kali Bromatum 6X, Lachesis Mutus 12X, 18X, 30X, Lithium Carbonicum 8X, 12X, 18X, 30X, Oenanthe Crocata 12X, Platinum Metallicum 18X, Pulsatilla (Pratensis) 12X, Serotonin (Hydrochloride) 8X, 12X, 30X, Stramonium 12X, Tarentula Hispana 16X, Thyroidinum (Suis) 8X, 12X, 30X, Zincum Metallicum 12X.

PURPOSE:

Aconitum Napellus – Mood Swings, Adrenalinum – Loss of Interest, Camphora - Grandiosity, Cimicifuga Racemosa – Racing Thoughts, Crocus Sativus - Guilt, Dopamine Hydrochloride – Excess Energy, Hyoscyamus Niger - Impulsiveness, Hypothalamus Suis – Racing Thoughts, Ignatia Amara – Mood Swings, Kali Bromatum - Inattention, Lachesis Mutus - Guilt, Lithium Carbonicum - Grandiosity, Oenanthe Crocata - Inattention, Platinum Metallicum – Excess Energy, Pulsatilla (Pratensis) - Impulsiveness, Serotonin (Hydrochloride) – Excess Energy, Stramonium – Mood Swings, Tarentula Hispana – Loss of Interest, Thyroidinum (Suis) - Guilt, Zincum Metallicum - Impulsiveness

USES:

• For the temporary relief of symptoms including:

• mood swings • loss of interest • guilt • grandiosity

• racing thoughts • excess energy • impulsiveness • inattention

These statements are based upon homeopathic principles. They have not been reviewed by the Food and Drug Administration.

WARNINGS:

If pregnant or breast-feeding, ask a health professional before use.

Keep out of reach of children. In case of overdose, contact a physician or Poison Control Center right away.

Tamper Evident: Sealed for your protection. Do not use if seal is broken or missing.

KEEP OUT OF REACH OF CHILDREN:

In case of overdose, contact a physician or Poison Control Center right away.

DIRECTIONS:

1-10 drops under the tongue, 3 times a day or as directed by a health professional. Consult a physician for use in children under 12 years of age.

INACTIVE INGREDIENTS:

Demineralized water, 25% ethanol

QUESTIONS:

Dist. By: Deseret Biologicals, Inc.
469 W. Parkland Drive
Sandy, UT 84070

www.desbio.com

800-827-8204

PACKAGE LABEL DISPLAY:

DesBio

Mood Swings

Homeopathic

NDC 43742-2205-1

1 FL OZ (30 ml)